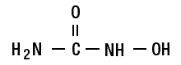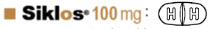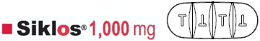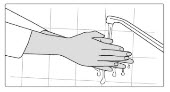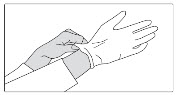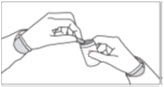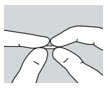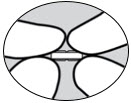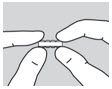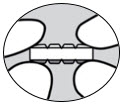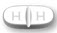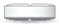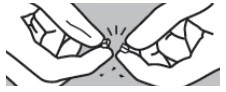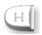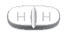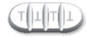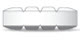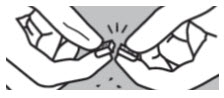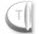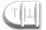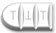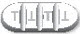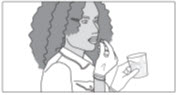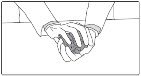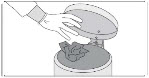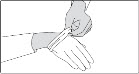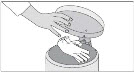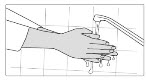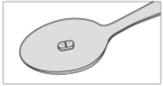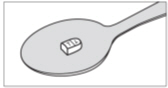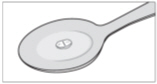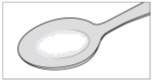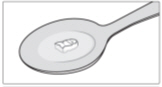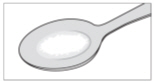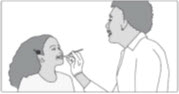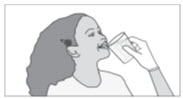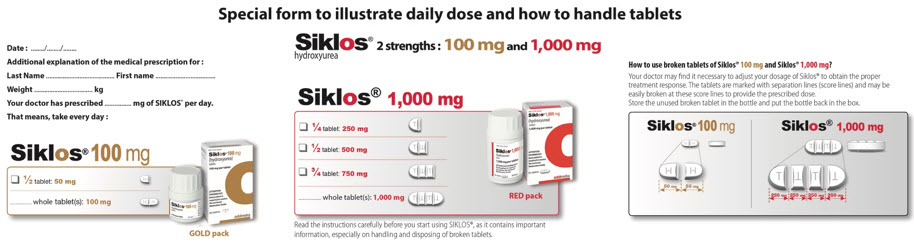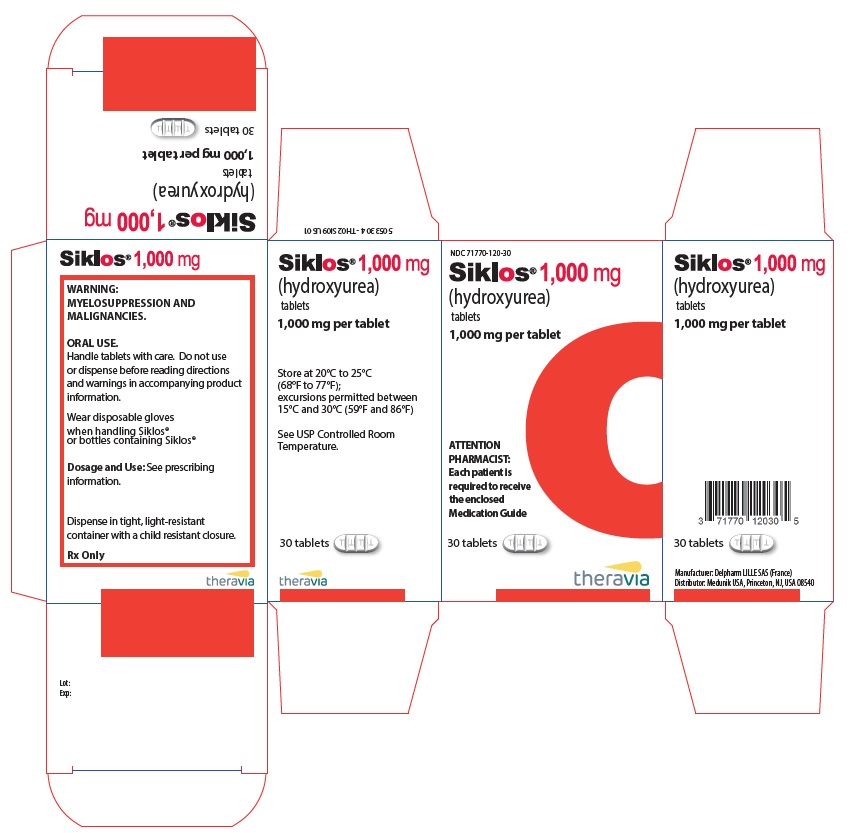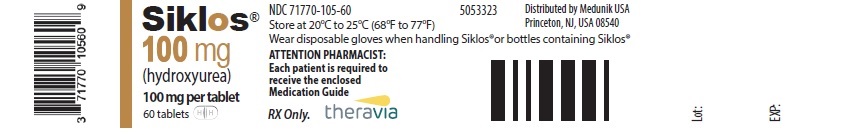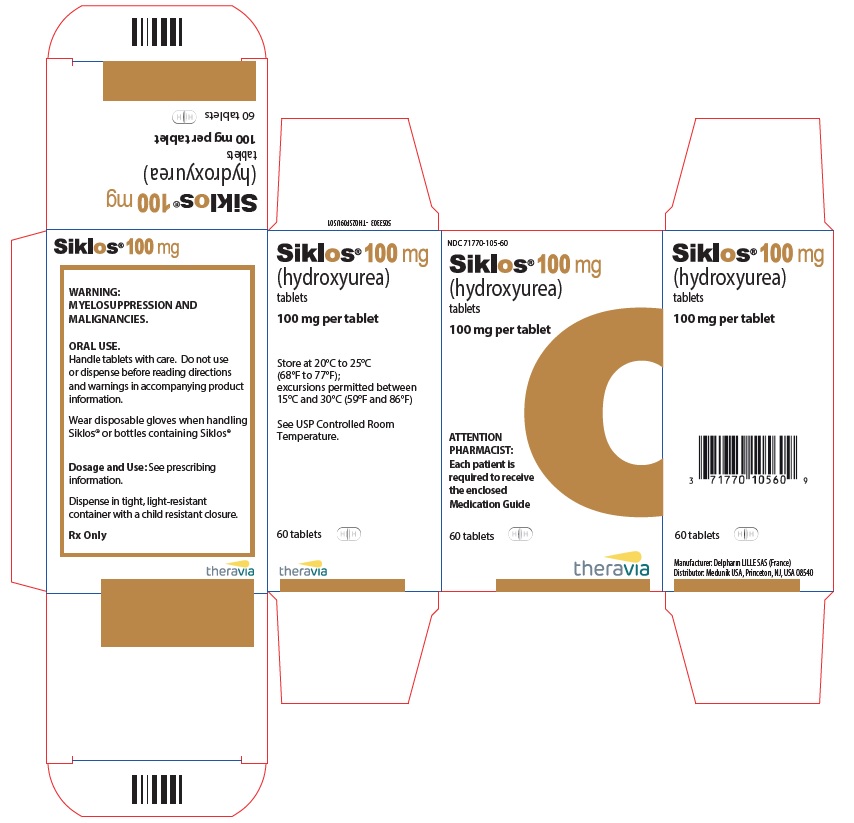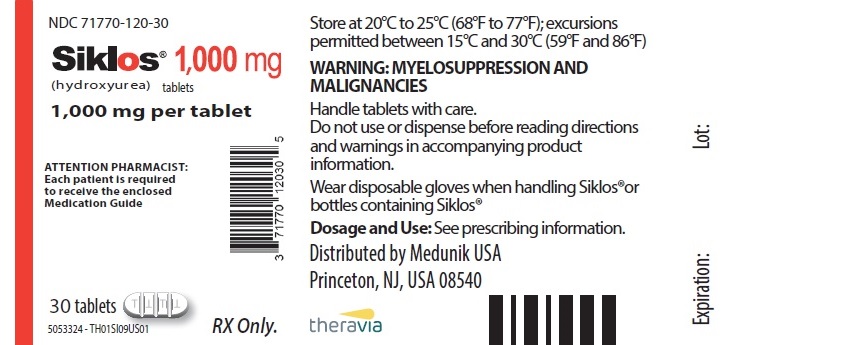 DRUG LABEL: Siklos
NDC: 71770-120 | Form: TABLET, FILM COATED
Manufacturer: Medunik
Category: prescription | Type: HUMAN PRESCRIPTION DRUG LABEL
Date: 20260107

ACTIVE INGREDIENTS: HYDROXYUREA 1000 mg/1 1
INACTIVE INGREDIENTS: MICROCRYSTALLINE CELLULOSE; SILICON DIOXIDE; SODIUM STEARYL FUMARATE; DIMETHYLAMINOETHYL METHACRYLATE - BUTYL METHACRYLATE - METHYL METHACRYLATE COPOLYMER; ISOPROPYL ALCOHOL

HIGHLIGHTS OF PRESCRIBING INFORMATION

These highlights do not include all the information needed to use SIKLOS safely and effectively. See full prescribing information for SIKLOS.
SIKLOS (hydroxyurea) tablets, for oral use
Initial U.S. Approval: 1967

WARNING: MYELOSUPPRESSION and MALIGNANCIES

See full prescribing information for complete boxed warning.

- Myelosuppression: SIKLOS may cause severe myelosuppression. Do not give if bone marrow function is markedly depressed. Monitor blood counts at baseline and throughout treatment. Interrupt treatment and reduce dose as necessary. (5.1)
- Malignancies: Hydroxyurea is carcinogenic. Advise sun protection and monitor patients for malignancies. (5.2)

RECENT MAJOR CHANGES

Warnings and Precautions, Test Interference (5.8) | 11/2023
Drug interactions, Test Interference (7.3) | 11/2023

1 INDICATIONS AND USAGE

SIKLOS is an antimetabolite, indicated to reduce the frequency of painful crises and to reduce the need for blood transfusions in adult and pediatric patients, 2 years of age and older, with sickle cell anemia with recurrent moderate to severe painful crises. (1)

2 DOSAGE AND ADMINISTRATION

Initial dose: 15 mg/kg in adults and 20 mg/kg in children once daily. Monitor blood counts every two weeks. (2.1)

- The dose may be increased by 5 mg/kg/day every 8 weeks, or sooner if a severe painful crisis occurs, until a maximum tolerated dose or 35 mg/kg/day is reached if blood counts are in an acceptable range. (2.1)
- Discontinue SIKLOS until hematologic recovery if blood counts are considered toxic. Resume treatment after reducing the dose by 5 mg/kg/day from the dose associated with hematological toxicity. (2.1)
- Renal impairment: Reduce the dose of SIKLOS by 50% in patients with creatinine clearance less than 60 mL/min. (2.2, 8.6, 12.3)

3 DOSAGE FORMS AND STRENGTHS

Tablets: functionally scored 100 mg and functionally triple-scored 1,000 mg tablet (3)

4 CONTRAINDICATIONS

Patients who have demonstrated a previous hypersensitivity to hydroxyurea or any other component of its formulation. (4)

5 WARNINGS AND PRECAUTIONS

- Embryo-Fetal toxicity: Can cause fetal harm. Advise of potential risk to a fetus and use of effective contraception. (5.3, 8.1, 8.3)
- Cutaneous vasculitic toxicities (incl. leg ulcers): Institute treatment and discontinue SIKLOS and/or reduce dose if this occurs. (5.4)
- Risks with concomitant use of antiretroviral drugs: Pancreatitis, hepatotoxicity, and neuropathy have occurred. Monitor for signs and symptoms patients with HIV infection using antiretroviral drugs; discontinue SIKLOS, and implement treatment. (5.5)
- Concomitant use with live virus vaccine: increased risk of severe infections. (5.6)
- Hemolytic Anemia: Monitor blood counts throughout treatment. If hemolysis persists, discontinue SIKLOS. (5.9)

6 ADVERSE REACTIONS

Most common adverse reactions to SIKLOS (incidence > 10%) include infections and neutropenia in children and infections and headache and dry skin in adults. (6)

To report SUSPECTED ADVERSE REACTIONS, contact the marketer Medunik at 1 844-884-5520 or FDA at 1-800-FDA-1088 or www.fda.gov/medwatch.

8 USE IN SPECIFIC POPULATIONS

Lactation: Advise women to stop breastfeeding while taking SIKLOS. (8.2)

FULL PRESCRIBING INFORMATION

WARNING: MYELOSUPPRESSION and MALIGNANCIES

Myelosuppression:SIKLOS may cause severe myelosuppression. Monitor blood counts at baseline and throughout treatment. Interrupt treatment and reduce dose as necessary [see Warnings and Precautions (5.1)] .

Malignancies:Hydroxyurea is carcinogenic. Advise sun protection and monitor patients for malignancies [see Warnings and Precautions (5.2)] .

1 INDICATIONS AND USAGE

SIKLOS®is indicated to reduce the frequency of painful crises and to reduce the need for blood transfusions in adult and pediatric patients, 2 years of age and older, with sickle cell anemia with recurrent moderate to severe painful crises

2 DOSAGE AND ADMINISTRATION

2.1 Recommended Dosing

The recommended SIKLOS dosing is described in Table 1.

Table 1: Dosing Recommendation Based on Blood Count
Dosing Regimen | Dose | Dose Modification Criteria | Monitoring Parameters
Initial Recommended Dosing | Adults: 15 mg/kg Pediatrics: 20 mg/kg once daily based on patient's actual or ideal weight, whichever is less. |  | Monitor the patient's blood count every 2 weeks [see Warnings and Precautions (5.1)] .
Dosing Adjustment Based on Blood Countsin an acceptable range | Increase dose 5 mg/kg/day every 8 weeks or if a painful crisis occurs. Give until mild myelosuppression (absolute neutrophil count 2,000/uL to 4,000/uL) is achieved, up to a maximum of 35 mg/kg/day. | Increase dosing only if blood counts are in an acceptable range. Increase dosing if a painful crisis occurs. Do not increase if myelosuppression occurs. | Blood Counts Acceptable Range: - neutrophils greater than or equal to 2,000 cells/mm^3 - platelets greater than or equal to 80,000/mm^3 - hemoglobin greater than 5.3 g/dL - reticulocytes greater than or equal to 80,000/mm^3if the hemoglobin concentration less than 9 g/dL
Dosing Adjustment Based on Blood Countsin a toxic range | Discontinue treatment. | If blood counts are considered toxic, discontinue SIKLOS until hematologic recovery. | Blood Counts Toxic Range: - neutrophils less than 2,000 cells/mm^3 younger patients with lower baseline counts may safely tolerate absolute neutrophil counts down to 1,250/mm^3. - platelets less than 80,000/mm^3 - hemoglobin less than 4.5 g/dL - reticulocytes less than 80,000/mm^3if the hemoglobin concentration less than 9 g/dL
Dosing After Hematologic Recovery | Reduce dose by 5 mg/kg/day. | Reduce the dose from the dose associated with hematologic toxicity. May titrate up or down every 8 weeks in 5 mg/kg/day increments. The patient should be at a stable dose with no hematologic toxicity for 24 weeks. Discontinue the treatment permanently if a patient develops hematologic toxicity twice.

Siklos is available in 100 mg and 1,000 mg tablets. The 100 mg tablets have 1 score line and can be split into 2 parts (each 50 mg). The 1,000 mg tablets have 3 score lines and can be split into 4 parts (each 250 mg). Therefore, the two strengths can be used to deliver doses of 1,000 mg, 750 mg, 500 mg, 250 mg, 100 mg, 50 mg and combinations thereof. Calculate the rounded doses to the nearest 50 mg or 100 mg strength based on clinical judgment.

Patients must be able to follow directions regarding drug administration and their monitoring and care.

Fetal hemoglobin (HbF) levels may be used to evaluate the efficacy of SIKLOS in clinical use. Obtain HbF levels every three to four months. Monitor for an increase in HbF of at least two-fold over the baseline value.

Administration:

The tablets should be taken once daily, at the same time each day, with a glass of water. For patients who are not able to swallow the tablets, these can be dispersed immediately before usein a small quantity of water in a teaspoon.

SIKLOS is a cytotoxic drug. Follow applicable special handling and disposal procedures [see References (15)].

2.2 Dose Modifications for Renal Impairment

Reduce the dose of SIKLOS by 50% in patients with creatinine clearance of less than 60 mL/min or with end-stage renal disease (ESRD) [see Use in Specific Populations (8.6)and Clinical Pharmacology (12.3)] . Obtain the creatinine clearance using a 24-hour urine collection.

Creatinine Clearance (mL/min) | Recommended SIKLOS Initial Dose (mg/kg daily)
 | Pediatrics | Adults
Greater than or equal to 60 | 20 | 15
Less than 60 or ESRD [On dialysis days, administer SIKLOS to patients with ESRD following hemodialysis] | 10 | 7.5

Monitor the hematologic parameters closely in these patients.

3 DOSAGE FORMS AND STRENGTHS

Tablets:

- 100 mg tablets: off-white, capsule-shaped, film-coated, functionally scored tablet with scoring on both sides which can be divided into two equal parts, each part is debossed with "H" on one side.
- 1,000 mg tablets: off-white, capsule-shaped, film-coated, functionally triple-scored tablet with scoring on both sides which can be divided into four equal parts, each part is debossed with "T" on one side.

4 CONTRAINDICATIONS

SIKLOS is contraindicated in:

- Patients who have demonstrated a previous hypersensitivity to hydroxyurea or any other component of its formulation [see Adverse Reactions (6)].

5 WARNINGS AND PRECAUTIONS

5.1 Myelosuppression

Hydroxyurea causes severe myelosuppression. Do not initiate treatment with hydroxyurea in patients if bone marrow function is markedly depressed. Bone marrow suppression may occur, and leukopenia is generally its first and most common manifestation. Thrombocytopenia and anemia occur less often, and are seldom seen without a preceding leukopenia.

Some patients, treated at the recommended initial dose of 15 mg/kg/day in adults or 20 mg/kg/day in children, have experienced severe or life-threatening myelosuppression. Due to the change in body weight requiring modification of daily dose, pediatric patients have an increased risk of myelosuppression at the time of dose adjustment.

Evaluate hematologic status prior to and every two weeks during treatment with SIKLOS. Provide supportive care and modify dose or discontinue SIKLOS as needed. Recovery from myelosuppression is usually observed within 15 days when therapy is interrupted. Resume therapy after interruption at a lower dose [see Dosage and Administration (2.1)] .

5.2 Malignancies

Hydroxyurea is a human carcinogen. In patients receiving long-term hydroxyurea for myeloproliferative disorders (a condition for which Siklos is not approved), secondary leukemia has been reported.

Leukemia secondary to long-term hydroxyurea has also been reported in patients with sickle cell disease. Leukemia has also been reported in patients with sickle cell disease and no prior history of treatment with hydroxyurea.

Skin cancer has also been reported in patients receiving long-term hydroxyurea. Advise protection from sun exposure and monitor for the development of secondary malignancies.

5.3 Embryo-Fetal Toxicity

Based on the mechanism of action and findings in animals, SIKLOS can cause fetal harm when administered to a pregnant woman. Hydroxyurea was embryotoxic and teratogenic in rats and rabbits at doses 0.8 times and 0.3 times, respectively, the maximum recommended human daily dose on a mg/m2 basis. Advise pregnant women of the potential risk to a fetus [see Use in Specific Populations (8.1)] .

Advise females of reproductive potential to use effective contraception during and after treatment with SIKLOS for at least 6 months after therapy. Advise males of reproductive potential to use effective contraception during and after treatment with SIKLOS for at least 6 months after therapy [see Use in Specific Populations (8.1, 8.3)] .

5.4 Vasculitic Toxicities (Including Leg Ulcers)

Cutaneous vasculitic toxicities, including vasculitic ulcerations and gangrene, have occurred in patients with myeloproliferative disorders during therapy with hydroxyurea. These vasculitic toxicities were reported most often in patients with a history of, or currently receiving, interferon therapy. Due to potentially severe clinical outcomes for the cutaneous vasculitic ulcers reported in patients with myeloproliferative disease (a condition for which SIKLOS is not approved), treatment with SIKLOS should be discontinued and/or its dose reduced if cutaneous vasculitic ulcerations develop. Rarely, ulcers are caused by leukocytoclastic vasculitis.

Avoid use of SIKLOS in patients with wounds on the legs (leg ulcers).

5.5 Risks with Concomitant Use of Antiretroviral Drugs

Pancreatitis, hepatotoxicity, and peripheral neuropathy have occurred when hydroxyurea was administered concomitantly with antiretroviral drugs, including didanosine and stavudine [see Drug Interactions (7.1)] .

5.6 Risks with Concomitant Use of Live Virus Vaccine

Avoid use of live virus vaccine in patients taking SIKLOS. Concomitant use of hydroxyurea with a live virus vaccine may potentiate the replication of the vaccine virus and/or may increase the adverse reactions of the vaccine virus and result in severe infections [see Drug Interactions (7.2)]. Patient's antibody response to vaccines may be decreased. Consider consultation with a specialist.

5.7 Macrocytosis

SIKLOS may cause macrocytosis, which is self-limiting, and is often seen early in the course of treatment. The morphologic change resembles pernicious anemia, but is not related to vitamin B12 or folic acid deficiency. This may mask the diagnosis of pernicious anemia. Prophylactic administration of folic acid is recommended.

5.8 Test Interference

Interference with Uric Acid, Urea, or Lactic Acid Assays is possible, rendering falsely elevated results of these in patients treated with hydroxyurea [see Drug Interactions (7.3)].

Hydroxyurea may falsely elevate sensor glucose results from certain continuous glucose monitoring (CGM) systems and may lead to hypoglycemia if sensor glucose results are relied upon to dose insulin.

If a patient using a CGM is to be prescribed hydroxyurea, consult with the CGM prescriber about alternative glucose monitoring methods.

5.9 Hemolytic Anemia

Cases of hemolytic anemia in patients treated with hydroxyurea for myeloproliferative diseases have been reported [see Adverse Reactions (6.1)] . Patients who develop acute jaundice or hematuria in the presence of persistent or worsening of anemia should have laboratory tests evaluated for hemolysis (e.g., measurement of serum lactate dehydrogenase, haptoglobin, reticulocyte, unconjugated bilirubin levels, urinalysis, and direct and indirect antiglobulin [Coombs] tests). In the setting of confirmed diagnosis of hemolytic anemia not related to the disease and in the absence of other causes, discontinue SIKLOS.

6 ADVERSE REACTIONS

The following clinically significant adverse reactions are described elsewhere in the labeling:

- Myelosuppression [see Warnings and Precautions (5.1)]
- Malignancies [see Warnings and Precautions (5.2)]
- Vasculitic toxicities (including Leg Ulcers) [see Warnings and Precautions (5.4)]
- Risks with concomitant use of antiretroviral drugs [see Warnings and Precautions (5.5)]
- Risk with concomitant use of live virus vaccine [see Warnings and Precautions (5.6)]
- Macrocytosis [see Warnings and Precautions (5.7)]
- Hemolytic Anemia [see Warnings and Precautions (5.9)]

6.1 Clinical Trial Experience

Because clinical trials are conducted under widely varying conditions, adverse reaction rates observed in the clinical trials of a drug cannot be directly compared to rates in the clinical trials of another drug and may not reflect the rates observed in practice.

The safety of SIKLOS has been assessed in 405 pediatric patients with sickle cell disease from 2-18 years of age and 1077 adults in the European Sickle Cell Disease prospective Cohort study ESCORT-HU.

The most frequently reported adverse reactions in ESCORT-HU were infections and myelosuppression, with mild to moderate neutropenia as the most common manifestation.

Other adverse reactions include skin and subcutaneous disorders (skin depigmentation/melanonychia, skin rash, alopecia), gastrointestinal disorders, vitamin D deficiency and headache.

At least one serious adverse reaction was reported in 33% of the 405 pediatric patients and 32% of the 1077 adults with sickle cell disease in ESCORT-HU. The most frequent serious adverse reactions were infections (18%), and blood and lymphatic system disorders (9%) in children, including serious neutropenia (3.2%), thrombocytopenia (3%) and anemia (3%). Other reported serious adverse reactions were gastrointestinal disorders (3.2 %), fever (2.5 %) and nervous system disorders (4%), including headache (2.7%). Among adults, the most frequent serious adverse reactions were infections (12.9%), respiratory, thoracic and mediastinal disorders (5.8%), blood and lymphatic disorders (4.8%), nervous system disorders (3.6%), and general disorders and administration site disorders (3.1%).

Table 2: Most frequent (greater than or equal to 2%) adverse reactions reported in pediatric patients enrolled in ESCORT-HU
Global Safety Set (N=405) | Total |  | Severity
Global Safety Set (N=405) | Total |  | Mild |  | Moderate |  | Severe
 | n | % | n | % | n | % | n | %
At least one adverse reaction | 261 | 64
Infections | 161 | 40 | 120 | 30 | 88 | 22 | 18 | 4.4
Other Infections | 92 | 23 | 66 | 16 | 32 | 8 | 3 | 0.7
Bacterial | 65 | 16 | 24 | 6 | 37 | 9 | 10 | 2.5
Viral | 40 | 10 | 23 | 6 | 14 | 3.5 | 3 | 0.7
Parvovirus B19 | 15 | 4 | 7 | 1.7 | 5 | 1.2 | 2 | 0.5
Blood and lymphatic system disorders | 85 | 21 | 51 | 13 | 59 | 15 | 14 | 3.5
Neutropenia | 51 | 13 | 26 | 6 | 31 | 8 | 4 | 1
Thrombocytopenia | 30 | 7 | 16 | 4 | 15 | 3.7 | 2 | 0.5
Anemia | 17 | 4.2 | 4 | 1 | 8 | 2 | 7 | 1.7
Gastrointestinal disorders | 53 | 13 | 29 | 7 | 30 | 7 | 4 | 1
Other Gastrointestinal Disorders | 30 | 7 | 13 | 3.2 | 15 | 3.7 | 2 | 0.5
Constipation | 10 | 2.5 | 5 | 1.2 | 5 | 1.2 | 0 | 0
Nausea | 10 | 2.5 | 4 | 1 | 4 | 1 | 2 | 0.5
Metabolic and nutrition disorders | 44 | 11 | 24 | 6 | 21 | 5 | 1 | 0.2
Deficiency of vitamin D | 25 | 6 | 19 | 4.7 | 7 | 1.7 | 1 | 0.2
Other Metabolic and nutrition disorders | 8 | 2 | 3 | 0.7 | 4 | 1 | 1 | 0.2
Weight gain | 8 | 2 | 1 | 0.2 | 7 | 1.7 | 0 | 0
Nervous system disorders | 45 | 11 | 19 | 4.7 | 19 | 4.7 | 8 | 2
Headache | 30 | 7 | 15 | 3.7 | 7 | 1.7 | 4 | 1
Other Nervous system disorders | 11 | 2.7 | 2 | 0.5 | 4 | 1 | 4 | 1
General disorders | 41 | 10 | 22 | 5 | 17 | 4.2 | 4 | 1
Fever | 31 | 8 | 20 | 4.9 | 12 | 3 | 2 | 0.5
Skin and subcutaneous tissue disorders | 38 | 9 | 29 | 7 | 14 | 3.5 | 1 | 0.2
Skin reactions | 15 | 4 | 8 | 2 | 7 | 1.7 | 1 | 0.2
Other Skin and subcutaneous tissue disorders | 13 | 3.2 | 8 | 2 | 5 | 1.2 | 0 | 0
Other Not SCD-related reactions | 23 | 6 | 16 | 4 | 3 | 0.7 | 1 | 0.2
Other Not SCD-related reactions | 23 | 6 | 16 | 4 | 3 | 0.7 | 1 | 0.2
Respiratory thoracic and mediastinal disorders | 11 | 3 | 6 | 1.5 | 3 | 0.7 | 2 | 0.5
Renal and urinary disorders | 8 | 2 | 2 | 0.5 | 4 | 1 | 0 | 0
n: number of patients with an adverse reaction

Table 3: Most frequent (greater than or equal to 3%) adverse reactions reported in adult patients enrolled in ESCORT-HU
Global adult safety set (N=1077) | Total |  | Severity
Global adult safety set (N=1077) | Total |  | Mild |  | Moderate |  | Severe
 | n | % | n | % | n | % | n | %
At least one adverse reaction | 897 | 84 | 586 | 54 | 617 | 57 | 345 | 32
Infections | 465 | 43 | 171 | 16 | 240 | 22 | 101 | 9
Viral infection | 47 | 4.4 | 17 | 1.6 | 21 | 1.9 | 5 | 0.5
Bacterial infection | 45 | 4.2 | 9 | 0.8 | 27 | 2.5 | 5 | 0.5
Bronchitis | 41 | 3.8 | 10 | 0.9 | 19 | 1.8 | 3 | 0.3
Influenza | 40 | 3.7 | 8 | 0.7 | 15 | 1.4 | 5 | 0.5
Urinary tract infection | 40 | 3.7 | 19 | 1.8 | 11 | 1.0 | 1 | 0.1
Nasopharyngitis | 40 | 3.7 | 21 | 1.9 | 13 | 1.2 | 1 | 0.1
Nervous system disorders | 313 | 29 | 131 | 12 | 125 | 12 | 54 | 5
Headache | 211 | 20 | 84 | 8 | 74 | 7 | 27 | 2.5
Dizziness | 100 | 9 | 43 | 4.0 | 32 | 3.0 | 9 | 0.8
General disorders and administration site conditions | 300 | 28 | 111 | 10 | 113 | 10 | 24 | 2.2
Asthenia | 100 | 9 | 30 | 2.8 | 18 | 1.7 | 10 | 0.9
Pyrexia | 91 | 8 | 27 | 2.5 | 39 | 3.6 | 4 | 0.4
Fatigue | 51 | 4.7 | 22 | 2.0 | 17 | 1.6 | 2 | 0.2
Edema peripheral | 33 | 3.1 | 9 | 0.8 | 13 | 1.2 | 2 | 0.2
Skin and subcutaneous tissue disorders | 297 | 28 | 160 | 15 | 123 | 11 | 23 | 2.1
Dry skin | 128 | 12 | 67 | 6.2 | 36 | 3.3 | 5 | 0.5
Skin ulcer | 80 | 7 | 19 | 1.8 | 44 | 4.1 | 11 | 1.0
Alopecia | 49 | 4.5 | 31 | 2.9 | 13 | 1.2 | 5 | 0.5
Gastrointestinal disorders | 267 | 25 | 116 | 11 | 110 | 10 | 25 | 2.3
Nausea | 69 | 6 | 28 | 2.6 | 26 | 2.4 | 3 | 0.3
Abdominal pain upper | 52 | 4.8 | 15 | 1.4 | 22 | 2.0 | 5 | 0.5
Diarrhea | 37 | 3.4 | 10 | 0.9 | 13 | 1.2
Respiratory, thoracic and mediastinal disorders | 256 | 24 | 70 | 7 | 103 | 10 | 48 | 4.5
Cough | 59 | 5.5 | 23 | 2.1 | 21 | 1.9 | 3 | 0.3
Lung disorder | 51 | 4.7 | 4 | 0.4 | 28 | 2.6 | 16 | 1.5
Dyspnea | 44 | 4.1 | 12 | 1.1 | 14 | 1.3 | 4 | 0.4
Blood and lymphatic system disorders | 250 | 23 | 74 | 7 | 121 | 11.2 | 61 | 6
Anemia | 103 | 10 | 11 | 1.0 | 51 | 4.7 | 37 | 3.4
Thrombocytopenia | 70 | 7 | 29 | 2.7 | 30 | 2.8 | 13 | 1.2
Neutropenia | 50 | 4.6 | 24 | 2.2 | 18 | 1.7 | 7 | 0.6
Musculoskeletal and connective tissue disorders | 247 | 23 | 93 | 9 | 101 | 9 | 25 | 2.3
Arthralgia | 95 | 9 | 26 | 2.4 | 31 | 2.9 | 7 | 0.6
Back pain | 48 | 4.5 | 11 | 1.0 | 18 | 1.7 | 6 | 0.6
Pain in extremity | 33 | 3.1 | 14 | 1.3 | 10 | 0.9
Investigations | 198 | 18 | 40 | 3.7 | 47 | 4.4 | 10 | 0.9
Weight increased | 43 | 4.0 | 15 | 1.4 | 22 | 2.0 | 4 | 0.4

6.2 Postmarketing Experience

The following adverse reactions have been identified during post-approval use of SIKLOS. Because these reactions are reported voluntarily from a population of uncertain size, it is not always possible to reliably estimate their frequency or establish a causal relationship to drug exposure.

- Blood and lymphatic system disorders: macrocytosis, hemolytic anemia in patients who are treated with hydroxyurea for myeloproliferative disorders.
- Gastrointestinal disorders:vomiting, gastrointestinal ulcer, severe hypomagnesemia
- Hepatobiliary disorders:elevation of hepatic enzymes
- Skin and subcutaneous tissue disorders:skin reactions (oral, ungula and cutaneous pigmentation), oral mucositis, rash, melanonychia,
- Reproductive system and breast disorders: oligospermia, azoospermia, amenorrhea

7 DRUG INTERACTIONS

7.1 Increased Toxicity with Concomitant Use of Antiretroviral Drugs

Pancreatitis

Pancreatitis (including fatal cases) have occurred in patients with HIV infection during therapy with hydroxyurea and didanosine, with or without stavudine. Hydroxyurea is not indicated for the treatment of HIV infection; however, if patients with HIV infection are treated with hydroxyurea, and in particular, in combination with didanosine and/or stavudine, monitor closely for signs and symptoms of pancreatitis. Permanently discontinue therapy with hydroxyurea in patients who develop signs and symptoms of pancreatitis.

Hepatotoxicity

Hepatotoxicity and hepatic failure resulting in death have been reported during postmarketing surveillance in patients with HIV infection treated with hydroxyurea and other antiretroviral drugs. Fatal hepatic events were reported most often in patients treated with the combination of hydroxyurea, didanosine, and stavudine. Avoid this combination.

Peripheral Neuropathy

Peripheral neuropathy, which was severe in some cases, has been reported in patients with HIV infection receiving hydroxyurea in combination with antiretroviral drugs, including didanosine, with or without stavudine.

7.2 Concomitant Use of Live Virus Vaccine

Concomitant use of SIKLOS with a live virus vaccine may potentiate the replication of the vaccine virus and/or may increase the adverse reactions of the vaccine virus, because normal defense mechanisms may be suppressed by SIKLOS therapy. Vaccination with a live vaccine in a patient taking SIKLOS may result in severe infections. Generally, the patient's antibody response to vaccines may be decreased. Treatment with SIKLOS and concomitant immunization with live virus vaccines should only be performed if benefits clearly outweigh potential risks. Consider consultation with a specialist.

7.3 Test Interference

Interference with Uric Acid, Urea, or Lactic Acid Assays

Studies have shown that there is an analytical interference of SIKLOS with the enzymes (urease, uricase, and lactate dehydrogenase) used in the determination of urea, uric acid, and lactic acid, rendering falsely elevated results of these in patients treated with SIKLOS.

Interference with Continuous Glucose Monitoring Systems

Hydroxyurea may falsely elevate sensor glucose results from certain continuous glucose monitoring (CGM) systems and may lead to hypoglycemia if sensor glucose results are relied upon to dose insulin.

If a patient using a CGM is to be prescribed hydroxyurea, consult with the CGM prescriber about alternative glucose monitoring methods.

8 USE IN SPECIFIC POPULATIONS

8.1 Pregnancy

Risk Summary

SIKLOS can cause fetal harm based on findings from animal studies and the drug's mechanism of action [see Clinical Pharmacology (12.1)] . There are no studies with the use of SIKLOS in pregnant women, and limited available data on SIKLOS use during pregnancy are insufficient to inform drug-associated risks. Drugs which affect DNA synthesis, such as hydroxyurea, may be potential mutagenic agents. In animal reproduction studies, administration of hydroxyurea to pregnant rats and rabbits during organogenesis produced embryotoxic and teratogenic effects at doses 0.8 times and 0.3 times, respectively, the maximum recommended human daily dose on a mg/m^2basis. In rats and rabbits, fetal malformations were observed with partially ossified cranial bones, absence of eye sockets, hydrocephaly, bipartite sternebrae, and missing lumbar vertebrae. Embryotoxicity was characterized by decreased fetal viability, reduced live litter sizes, and developmental delays (see Data) . Advise pregnant women of the potential risk to a fetus (see Clinical Considerations).

Background risk of major birth defects and miscarriage for the indicated population are unknown. All pregnancies have a background risk of birth defect, loss, or other adverse outcomes. In the U.S. general population, the estimated background risk of major birth defects and miscarriage in clinically recognized pregnancies is 2%–4% and 15%–20%, respectively.

Clinical Considerations

Fetal/Neonatal adverse reactions

Although the data on a limited number of exposed pregnancies indicate no adverse effects on pregnancy or on the health of the fetus/newborn, patients on SIKLOS should be made aware of the potential risks to the fetus.

Based on the limited amount of available information, in case of an exposure to SIKLOS of pregnant female patients or pregnant partners of male patients, treated by SIKLOS, a careful follow-up with adequate clinical, biological and ultrasonographic examinations should be considered.

Data

Human Data

According to a retrospective analysis of a cohort of 123 adult patients treated with hydroxyurea, twenty-three pregnancies have been reported from 15 women treated with hydroxyurea and partners of 3 men not using barrier contraception treated with hydroxyurea. Most (61%) had no adverse developmental outcomes. In the other cases with known evolution, pregnancy had been interrupted either voluntarily or upon medical advice.

In retrospective cohorts of 352 children and adolescents with sickle cell disease older than 2 years treated with hydroxyurea for a period of up to 12 years, 3 pregnancies under hydroxyurea were reported with no adverse developmental outcomes.

From post-marketing data of SIKLOS, 3 pregnancies have been reported while the father was treated with SIKLOS and 16 pregnancies have been reported in 15 females treated with SIKLOS. Among the 13 cases with known evolution, 5 pregnancies had no adverse developmental outcomes, 4 led to premature birth, and 4 were early terminated.

Animal Data

Hydroxyurea has been demonstrated to be a potent teratogen in a wide variety of animal models, including mice, hamsters, cats, miniature swine, dogs, and monkeys at doses within 1-fold of the human dose given on a mg/m^2basis. Hydroxyurea is embryotoxic and causes fetal malformations (partially ossified cranial bones, absence of eye sockets, hydrocephaly, bipartite sternebrae, missing lumbar vertebrae) at 180 mg/kg/day (about 0.8 times the maximum recommended human daily dose on a mg/m^2basis) in rats and at 30 mg/kg/day (about 0.3 times the maximum recommended human daily dose on a mg/m^2basis) in rabbits. Embryotoxicity was characterized by decreased fetal viability, reduced live litter sizes, and developmental delays. Hydroxyurea crosses the placenta. Single doses of ≥375 mg/kg (about 1.7 times the maximum recommended human daily dose on a mg/m^2basis) to rats caused growth retardation and impaired learning ability.

8.2 Lactation

Risk Summary

It is not known whether SIKLOS is excreted in human milk, the effects of SIKLOS on the breastfed child, or the effects of SIKLOS on milk production. Because of the potential for serious adverse reactions in a breastfed child from SIKLOS, including carcinogenicity, advise patients not to breastfeed during treatment with SIKLOS.

8.3 Females and Males of Reproductive Potential

Pregnancy Testing

SIKLOS can cause fetal harm when administered to a pregnant woman [see Use in Specific Populations (8.1)] .

Verify the pregnancy status of females of reproductive potential prior to initiating SIKLOS therapy.

Contraception

Females

Advise females of reproductive potential to use effective contraception during and after treatment with SIKLOS for at least 6 months after therapy. Advise females to immediately report pregnancy.

Males

SIKLOS may damage spermatozoa and testicular tissue, resulting in possible genetic abnormalities. Males with female sexual partners of reproductive potential should use effective contraception during and after treatment with SIKLOS for at least 6 months after therapy [see Nonclinical Toxicology (13.1)] .

Infertility

Males

Based on findings in animals and humans, male fertility may be compromised by treatment with SIKLOS. Azoospermia or oligospermia, sometimes reversible, has been observed in men. Before the start of therapy, inform male patients about the possibility of sperm conservation [see Adverse Reactions (6)and Nonclinical Toxicology (13.1)] .

8.4 Pediatric Use

The safety and effectiveness of SIKLOS have been established in pediatric patients aged 2-18 years with sickle cell anemia with recurrent moderate to severe painful crises. Use of SIKLOS in these age groups is supported by evidence from a non-interventional cohort study, the European Sickle Cell Disease prospective Cohort study, ESCORT-HU, in which 405 pediatric patients ages 2 to <18 were enrolled. Among the 405 pediatric patients treated with SIKLOS, 274 were children (2-11) and 108 were adolescents (12-16) [see Clinical Studies (14)] .

Continuous follow-up of the growth of treated children is recommended.

Pediatric patients aged 2-16 years had a higher risk of neutropenia than patients more than 16 years old.

The safety and effectiveness of SIKLOS have not been established in pediatric patients less than 2 years of age.

8.6 Renal Impairment

The exposure to SIKLOS is higher in patients with creatinine clearance of less than 60 mL/min. Reduce dosage and closely monitor the hematologic parameters when SIKLOS is to be administered to these patients [see Dosage and Administration (2.2)and Clinical Pharmacology (12.3)] .

8.7 Hepatic Impairment

Monitor hematologic parameters more frequently in patients with hepatic impairment receiving SIKLOS.

10 OVERDOSAGE

Acute mucocutaneous toxicity has been reported in patients receiving hydroxyurea at doses several times above the therapeutic dose. Soreness, violet erythema, oedema on palms and soles followed by scaling of hand and feet, severe generalized hyperpigmentation of the skin and stomatitis have been observed. In patients with sickle cell anemia, neutropenia was reported in isolated cases of hydroxyurea overdose (1.43 times and 8.57 times of the maximum recommended dose of 35 mg/kg b.w./day). Monitor blood counts weekly until recovery. Treatment of overdose consists of gastric lavage, followed by symptomatic treatment and control of bone marrow function.

11 DESCRIPTION

SIKLOS (hydroxyurea) is an antimetabolite that is available for oral use as functionally scored 100 mg film-coated tablet and functionally triple-scored 1,000 mg film-coated tablet containing 100 and 1,000 mg of hydroxyurea, respectively. Inactive ingredients include silicified microcrystalline cellulose, sodium stearyl fumarate, and film-coating agent amino methacrylate copolymer.

Hydroxyurea is a white crystalline powder. It has a molecular weight of 76.05. Its structural formula is:

12 CLINICAL PHARMACOLOGY

12.1 Mechanism of Action

The precise mechanism by which hydroxyurea produces its cytotoxic and cytoreductive effects is not known. However, various studies support the hypothesis that hydroxyurea causes an immediate inhibition of DNA synthesis by acting as a ribonucleotide reductase inhibitor, without interfering with the synthesis of ribonucleic acid or of protein.

The mechanisms by which SIKLOS produces its beneficial effects in patients with sickle cell Anemia (SCA) are uncertain. Known pharmacologic effects of SIKLOS that may contribute to its beneficial effects include increasing hemoglobin F levels in red blood cells (RBCs), decreasing neutrophils, increasing the water content of RBCs, increasing deformability of sickled cells, and altering the adhesion of RBCs to endothelium.

12.2 Pharmacodynamics

The correlation between hydroxyurea concentrations, reduction of crisis rate, and increase in HbF, is not known.

12.3 Pharmacokinetics

Mean peak plasma concentrations and AUCs increase more than proportionally with increase of dose. There is no drug accumulation upon once daily dosing of hydroxyurea.

Absorption

Following oral administration, hydroxyurea reaches peak plasma concentrations in 1 to 4 hours. The oral bioavailability of hydroxyurea was reported to be 85 -100%.

Effect of Food

There are no data on the effect of food on the absorption of hydroxyurea.

Distribution

Hydroxyurea distributes throughout the body with a volume of distribution approximating total body water. Hydroxyurea concentrates in leukocytes and erythrocytes.

Elimination

Half-life of hydroxyurea is about 2-4 hours.

Metabolism

Up to 60% of an oral dose undergoes conversion through saturable hepatic metabolism and a minor pathway of degradation by urease found in intestinal bacteria.

Excretion

The percentage of the dose excreted in urine was approximately 40% in pediatric patients with sickle cell anemia.

Specific Populations

Patients with Renal Impairment

The effect of renal impairment on the pharmacokinetics of hydroxyurea was assessed in adult patients with sickle cell anemia and renal impairment. Patients with normal renal function (creatinine clearance [CrCl] >80 mL/min), mild (CrCl 50-80 mL/min), moderate (CrCl =30-<50 mL/min), or severe (<30 mL/min) renal impairment received a single oral dose of 15 mg/kg hydroxyurea. Creatinine clearance values were obtained using 24-hour urine collections. Patients with ESRD received two doses of 15 mg/kg separated by 7 days; the first was given following a 4-hour hemodialysis session, the second prior to hemodialysis. The exposure to hydroxyurea (mean AUC) in patients with CrCl <60 mL/min and those with ESRD was 64% higher than in patients with normal renal function (CrCl >60 mL/min). Reduce the dose of SIKLOS when it is administered to patients with creatinine clearance of <60 mL/min or with ESRD following hemodialysis [see Dosage and Administration (2.2)and Use in Specific Populations (8.6)].

Patients with Hepatic impairment

There are no data that support specific guidance for dose adjustment in patients with hepatic impairment.

Pediatric Patients

The pharmacokinetics of hydroxyurea is similar between children (4 to 17 years) and adults.

13 NONCLINICAL TOXICOLOGY

13.1 Carcinogenesis, Mutagenesis, Impairment of Fertility

Conventional long-term studies to evaluate the carcinogenic potential of hydroxyurea have not been performed. However, hydroxyurea is presumed to be a transspecies carcinogen. Intraperitoneal administration of 125 to 250 mg/kg hydroxyurea (about 0.6-1.2 times the maximum recommended human oral daily dose on a mg/m^2basis) thrice weekly for 6 months to female rats increased the incidence of mammary tumors in rats surviving to 18 months compared to control. Hydroxyurea is mutagenic in vitroto bacteria, fungi, protozoa, and mammalian cells. Hydroxyurea is clastogenic in vitro(hamster cells, human lymphoblasts) and in vivo(SCE assay in rodents, mouse micronucleus assay). Hydroxyurea causes the transformation of rodent embryo cells to a tumorigenic phenotype [see Warnings and Precautions (5.2, 5.3)].

Hydroxyurea administered to male rats at 60 mg/kg /day (about 0.3 times the maximum recommended human daily dose on a mg/m^2basis) produced testicular atrophy, decreased spermatogenesis and significantly reduced their ability to impregnate females [see Use in Specific Populations (8.3)].

14 CLINICAL STUDIES

Pediatric Patients with Sickle Cell Disease

The efficacy of SIKLOS was assessed in the European Sickle Cell Disease Cohort study (ESCORT HU) [NCT02516579]. This is an open-label single-arm study of 405 pediatric patients with sickle cell disease from 2-18 years of age, of which 141 had not been previously treated with hydroxyurea prior to enrollment. Evaluable patients had at least 12 months follow-up (median [range] 23 months [12,80]). Median (range) hemoglobin F percentages were 5.6% (1.3, 15.0) at baseline and 12.8% (2.1, 37.2) at least 6 months (the value closest to 6 months collected between 5 and 14 months) after initiation of SIKLOS treatment, with median (range) change of 5.9% (-2.2, 34.7) in 47 patients. Median (range) hemoglobin levels were 8.2 g/dL (3.7, 14.2) at baseline, 8.8 g/dL (0.7, 13.1) at 6 months (the value closest to 6 months collected between 5 and 7 months), and 8.9 g/dL (5.5, 13.2) at 12 months (the value closest to 12 months collected between 10 and 14 months) after initiation of SIKLOS treatment. The median (range) change was 0.5 g/dL (-4.6, 6.1) in 63 patients at 6 months (the post-baseline value closest to 6 months collected between 5 and 7 months) and 0.7 g/dL (-6.4, 6.0) in 83 patients at 12 months (the post-baseline value closest to 12 months collected between 10 and 14 months) after initiation of SIKLOS treatment.

Among pediatric patients not previously treated with hydroxyurea prior to enrollment and analyzable for efficacy (N=141), the percentage of patients with at least one vaso-occlusive episode, one episode of acute chest syndrome, one hospitalization due to SCD or one blood transfusion decreased after 12 months of SIKLOS treatment (Table 4).

Table 4: Comparison of SCD Events in the First Year of Treatment with SIKLOS with SCD Events in the 12 Months Prior to Enrollment – ESCORT HU Trial (N=141) in Pediatric Patients
SCD events | Patients under 18 years old previously not treated with hydroxyurea with at least 12 months follow-up data available for clinical efficacy (N=141)
SCD events | In the 12 months prior to enrolment | After 12 months of Siklos®treatment | Change
Number of patients with at least one vaso-occlusive episode (in 120 evaluable patients)
No | 37 (31%) | 69 (57.5%)
Yes | 83 (69%) | 51 (42.5%)
Number of vasoocclusive episodes over 12 months (in 113 evaluable patients)
Median (range) | 2 (0, 1) | 0 (0.0, 7.0) | -1 (-10.0, 5.0)
Number of patients with at least one episode of acute chest syndrome (in 123 evaluable patients)
No | 94 (76%) | 116 (94%)
Yes | 29 (24%) | 7 (6%)
Number of episodes of acute chest syndrome over 12 months (in 123 evaluable patients)
Median (range) | 0 (0.0, 2.0) | 0 (0.0, 1.0) | 0 (-2.0, 1.0)
Number of patients with at least one hospitalization related to SCD (in 110 evaluable patients)
No | 27 (25%) | 64 (58%)
Yes | 83 (75%) | 46 (42%)
Number of hospitalizations related to SCD over 12 months (in 106 evaluable patients)
Median (range) | 2 (0.0, 6.0) | 0 (0.0, 7.0) | -1 (-6.0, 6.0)
Number of days of hospitalizations related to SCD over 12 months (in 100 evaluable patients)
Median (range) | 8 (0.0, 58.0) | 0 (0.0, 100.0) | -3 (-58.0, 86.0)
Number of patients with at least one blood transfusion (in 122 evaluable patients)
No | 66 (54%) | 94 (77%)
Yes | 56 (46%) | 28 (23%)

Adult Patients with Sickle Cell Disease

In ESCORT-HU 1077 adult patients were included of which 436 patients were naïve to HU treatment. There were 370 evaluable patients who had at least 12 months follow-up (Median [range] 41 months [29, 54].

Median (range) hemoglobin F percentages were 5.2% (0.2, 30.9) at baseline and 14.2% (0.5, 41.5) at least 6 months (the value closest to 6 months collected between 5 and 14 months) after initiation of SIKLOS treatment, with a median (range) change of 8% (-8.0, 33.3) in 181 patients. Among adult patients previously not treated with hydroxyurea prior to enrollment and analyzable for efficacy (N=370), the incidence and number of vaso-occlusive events, hospitalizations, acute chest syndrome and blood transfusions in the 12 month period before treatment and after initiation of treatment decreased after 12 months of SIKLOS treatment. Table 5 provides the efficacy results for ESCORT-HU.

Table 5: Comparison of SCD Events in the First Year of Treatment with SIKLOS with SCD Events in the 12 Months Prior to Enrollment – ESCORT HU Trial (N=370) in Adult Patients
SCD events | Adult Patients previously not treated with hydroxyurea with at least 12 months follow-up data available for clinical efficacy (N=369)
SCD events | In the 12 months prior to enrolment | After 12 months of Siklos®treatment | Change
Number of patients with at least one vaso-occlusive episode (in 367 evaluable patients)
No | 133 (36.2%) | 226 (61.6%)
Yes | 234 (63.8%) | 141 (38.4%)
Number of vasoocclusive episodes over 12 months (in 343 evaluable patients)
Median (range) | 1.0 (0.0, 20.0) | 0.0 (0.0, 30.0) | 0.0 (-20.0, 24.0)
Number of patients with at least one episode of acute chest syndrome (in 365 evaluable patients)
No | 273 (74.8%) | 338 (92.6%)
Yes | 92 (25.2%) | 27 (7.4%)
Number of episodes of acute chest syndrome over 12 months (in 364 evaluable patients)
Median (range) | 1.0 (0.0, 5.0) | 0.0 (0.0, 3.0) | 0.0 (-5.0 ; 2.0)
Number of patients with at least one hospitalization related to SCD (in 366 evaluable patients)
No | 152 (41.5%) | 252 (68.9%)
Yes | 214 (58.5%) | 114 (31.1%)
Number of hospitalizations related to SCD over 12 months (in 360 evaluable patients)
Median (range) | 1 (0.0, 15.0) | 0 (0.0, 10.0) | 0 (-15.0, 8.0)
Number of days of hospitalizations related to SCD over 12 months (in 313 evaluable patients)
Median (range) | 2 (0.0, 90.0) | 0 (0.0, 77.0) | 0 (-90.0, 57.0)
Number of patients with at least one blood transfusion (in 365 evaluable patients)
No | 207 (56.7%) | 296 (81.1%)
Yes | 158 (43.3%) | 69 (18.9%)

15 REFERENCES

OSHA Hazardous Drugs. OSHA.http://www.osha.gov/SLTC/hazardousdrugs/index.html.

16 HOW SUPPLIED/STORAGE AND HANDLING

16.1 How Supplied

SIKLOS (hydroxyurea) film-coated tablet is supplied in high density polyethylene (HDPE) bottle with polypropylene child-resistant cap with a desiccant unit containing 30 (SIKLOS 1,000 mg) or 60 (SIKLOS 100 mg) film coated tablets. Each bottle containing SIKLOS 100 mg tablets or SIKLOS 1000 mg tablets is supplied in a carton.

SIKLOS is supplied in the following strengths:

- 100 mg off-white, capsule-shaped, film-coated, functionally scored tablet with scoring on both sides which can be divided into two equal parts, each part is debossed with "H" on one side.
- 1,000 mg off-white, capsule-shaped, film-coated, functionally triple-scored tablet with scoring on both sides which can be divided into four equal parts, each part is debossed with "T" on one side.

 | Bottles of 30 | Bottles of 60
100 mg | N/A | NDC 71770-105-60
1,000 mg | NDC 71770-120-30 | N/A

16.2 Storage

Store at 20°C to 25°C (68°F to 77°F); excursions permitted between 15°C and 30°C (59°F and 86°F) [see USP Controlled Room Temperature]. Keep tightly closed.

Broken tablets must be stored in the bottle and must be used within three months.

16.3 Handling and Disposal

SIKLOS is a cytotoxic drug. Follow applicable special handling and disposal procedures [see References (15)] .

To decrease the risk of contact, advise caregivers to wear disposable gloves when handling SIKLOS or bottles containing SIKLOS. Wash hands with soap and water before and after contact with the bottle or tablets when handling SIKLOS. Avoid exposure to crushed tablets. If contact with crushed tablets occurs on the skin, wash affected area immediately and thoroughly with soap and water. If contact with crushed tablets occurs on the eye(s), the affected area should be flushed thoroughly with water or isotonic eyewash designated for that purpose for at least 15 minutes.

Powder spilled from the broken tablet should be wiped up with a damp disposable towel which must be thrown away in a closed container such as a plastic bag to avoid ingestion of powder by other people. The spill areas should then be cleaned using a detergent solution followed by clean water.

17 PATIENT COUNSELING INFORMATION

Advise the patient or caregiver to read the FDA-approved patient labeling (Instructions for Use and Medication Guide).

- There is a risk of myelosuppression. Emphasize the importance of monitoring blood counts every two weeks throughout the duration of therapy to patients taking SIKLOS [see Warnings and Precautions (5.1)] . Advise patients to report signs and symptoms of infection or bleeding immediately.
- Advise patients that there is a risk of cutaneous vasculitic toxicities and secondary malignancies including leukemia. Advise use of sun protection [see Warnings and Precautions (5.1)] .
- Advise females of reproductive potential of the potential risk to a fetus should they become pregnant while taking SIKLOS. Advise patients to inform their healthcare provider of a known or suspected pregnancy. Advise females and males of reproductive potential to use contraception during and after treatment with SIKLOS [see Warnings and Precautions (5.3)and Use in Specific Populations (8.1, 8.3)] .
- Advise females to discontinue breastfeeding during treatment with SIKLOS [see Use in Specific Populations (8.2)] .
- Advise male patients of potential risk to fertility [see Use in Specific Populations (8.3)] .
- Advise patients with HIV infection to contact their physician for signs and symptoms of pancreatitis, hepatic events, and peripheral neuropathy [see Warnings and Precautions (5.5)] .
- Advise patients to notify their healthcare provider if they are using a continuous glucose monitoring system while taking SIKLOS [see Warnings and Precautions (5.8)].
- Advise patients of the risk of hemolytic anemia. Advise patients that they will have blood tests to evaluate for this if they develop persistent anemia not related to sickle cell anemia [see Warnings and Precautions (5.9)] .
- Because SIKLOS tablets are scored, advise patients on how to take SIKLOS properly.

Distributed by:
Medunik USA, 2 Research Way, suite 1B, Princeton, NJ 08540.
Manufactured for. Theravia: 16 rue Montrosier 92200 Neuilly-sur-Seine France
Manufactured by: Delpharm Lille, 22 rue de Toufflers 59452 Lys Lez Lannoy France

SIKLOS is a trademark of Theravia.

MEDICATION GUIDE
SIKLOS (See – k – los)
(hydroxyurea)
tablets

What is the most important information I should know about SIKLOS?

SIKLOS can cause serious side effects including:

- Low blood cell counts are common with SIKLOS, including low red blood cells, white blood cells, and platelets, and can be severe and life-threatening. If your white blood cell count becomes very low, you are at increased risk for infection.Your healthcare provider will check your blood cell counts before and every 2 weeks during treatment with SIKLOS. Your healthcare provider may change your dose or tell you to stop taking SIKLOS if you have low blood cell counts. Tell your healthcare provider right away if you get any of the following symptoms:

- fever or chills
- body aches
- feeling very tired

- shortness of breath
- unusual headache
- bleeding or unexplained bruising

- Cancer.Some people have developed cancer, such as leukemia and skin cancer, after taking SIKLOS for a long time. Your healthcare provider will check you for cancer. You should protect your skin from the sun using sunblock, hats, and sun-protective clothing.
- SIKLOS can harm your unborn baby.
  For females taking SIKLOS who can become pregnant:
  - You should talk with your healthcare provider about the risks of SIKLOS to your unborn baby.
  - You should use effective birth control during treatment with SIKLOS and for at least 6 months after treatment with SIKLOS.
  - Your healthcare provider will perform a pregnancy test before you start treatment with SIKLOS. Tell your healthcare provider right away if you become pregnant or think you may be pregnant.
  For males taking SIKLOS:SIKLOS can affect your sperm. If you have a female sexual partner who can become pregnant, you should use effective birth control during treatment with SIKLOS and for at least 6 months after treatment.
  SIKLOS may cause fertility problems in males. Talk to your healthcare provider if this is a concern for you.

See " What are the possible side effects of SIKLOS?" for more information about side effects.

What is SIKLOS?
SIKLOS is a prescription medicine that is used to reduce the frequency of painful crises and reduce the need for blood transfusions in adults and children, 2 years of age and older, with sickle cell anemia with recurrent moderate to severe painful crises.
It is not known if SIKLOS is safe and effective in children less than 2 years of age.

Do not take SIKLOS if you are allergic to hydroxyurea or any of the ingredients in SIKLOS. See the end of this Medication Guide for a list of the ingredients in SIKLOS.

Before taking SIKLOS, tell your healthcare provider about all of your medical conditions, including if you:

- have kidney problems or are receiving hemodialysis
- have liver problems
- have human immunodeficiency virus (HIV) or take HIV medicines. Taking SIKLOS with certain HIV medicines can cause serious reactions and may lead to death.
- have increased levels of uric acid in your blood (hyperuricemia)
- have a history of receiving interferon therapy or are currently receiving interferon therapy
- have leg wounds or ulcers
- plan to receive any vaccinations. You should not receive "live vaccines" during treatment with SIKLOS.
- are pregnant or plan to become pregnant. See " What is the most important information I should know about SIKLOS?"
- are breastfeeding or plan to breastfeed. It is not known if SIKLOS can pass into your breast milk. Do not breastfeed during treatment with SIKLOS.
- are using a continuous glucose monitor (CGM) to test your blood glucose. Hydroxyurea may affect your sensor glucose results and may lead to low blood sugar (hypoglycemia). Talk to the healthcare provider that prescribed your CGM about whether it is safe to use while you are taking SIKLOS.

Tell your healthcare provider about all the medicines you take, including prescription and over-the-counter medicines, vitamins, and herbal supplements.

How should I take SIKLOS?

Read the Instructions for Use at the end of this Medication Guide for step-by-step instructions on how to prepare a dose of SIKLOS. If you have any questions, talk to your healthcare provider or pharmacist.

- Take SIKLOS exactly as your healthcare provider tells you to take it.
- Take SIKLOS 1 time a day at the same time each day.
- Swallow the tablet(s) with a glass of water. If you are not able to swallow SIKLOS tablets, you can dissolve your prescribed dose in a small amount of water in a teaspoon and swallow right away.
- SIKLOS is supplied as 100 mg tablets and 1,000 mg tablets. The SIKLOS tablets have separation lines (score lines) and can be broken at these score lines to provide smaller doses.
  - Each 100 mg tablet can be divided into 2 equal parts (each part is 50 mg).
  - Each 1,000 mg tablet can be divided into 4 equal parts (each part is 250 mg).
- Your healthcare provider will tell you how many tablets or parts of a tablet you should take.
- SIKLOS tablets must be handled with care. To decrease the risk of exposure, you or your caregivers should do the following when handling SIKLOS:
  - Wear disposable gloves when handling SIKLOS or bottles containing SIKLOS. Wash your hands with soap and water before and after handling SIKLOS tablets or bottles containing SIKLOS.
  - Avoid contact with crushed tablets. If contact with crushed tablets happens on the skin, wash the skin area right away and thoroughly with soap and water. If contact with crushed tablets happens in the eyes, flush the eyes thoroughly with water or isotonic eyewash used for that purpose for at least 15 minutes.
  - Powder spilled from the broken tablet should be wiped up with a damp disposable towel which must be thrown away in a closed container such as a plastic bag to avoid ingestion of powder by other people. The spill areas should then be cleaned using a detergent solution followed by clean water.
- If you take too much SIKLOS, call your healthcare provider or go to the nearest hospital emergency room right away.

What are the possible side effects of SIKLOS?
SIKLOS may cause serious side effects, including:
See " What is the most important information I should know about SIKLOS?"

- Skin ulcers, including leg ulcers, and death of skin tissue (gangrene)have happened in people who take SIKLOS. This has happened most often in people who receive interferon therapy or have a history of interferon therapy. Your healthcare provider will decrease your dose or stop treatment with SIKLOS if you develop any skin ulcers.
- Enlarged red blood cells (macrocytosis). Macrocytosis is common in people who take SIKLOS and can make it difficult to detect a decrease of folic acid. Your healthcare provider may prescribe a folic acid supplement for you.
- Hemolytic Anemia,the fast breakdown of red blood cells, has happened in people who take SIKLOS. Tell your healthcare provider if you develop yellowing of your skin (jaundice) or blood in your urine. Your healthcare provider may do blood tests if you have persistent or worsening anemia.

The most common side effects of SIKLOS in children include:

- infections
- low white blood cells

The most common side effects of SIKLOS in adults include:

- infections
- headache
- dry skin

These are not all the possible side effects of SIKLOS.
Call your doctor for medical advice about side effects. You may report side effects to FDA at 1-800-FDA-1088.

How should I store SIKLOS?

- Store SIKLOS at room temperature between 68°F to 77°F (20°C to 25°C).
- Keep the SIKLOS bottle tightly closed.
- Broken SIKLOS tablets must be stored in the bottle and must be used within three months.

Keep SIKLOS and all medicines out of the reach of children.

General information about the safe and effective use of SIKLOS.
Medicines are sometimes prescribed for purposes other than those listed in a Medication Guide. Do not use SIKLOS for a condition for which it was not prescribed. Do not give SIKLOS to other people, even if they have the same symptoms you have. It may harm them. You can ask your healthcare provider or pharmacist for information about SIKLOS that is written for health professionals.

What are the ingredients of SIKLOS?
Active ingredient:hydroxyurea
Inactive ingredients:silicified microcrystalline cellulose, sodium stearyl fumarate, and film-coating agent amino methacrylate copolymer.
Distributed by: Medunik USA, 2 Research Way, suite 1B, Princeton, NJ 08540.
Manufactured for:. Theravia : 16 rue Montrosier 92200 Neuilly-sur-Seine, France
Manufactured by: Delpharm Lille, 22 rue de Toufflers 59452 Lys Lez Lannoy France.
SIKLOS is a trademark of Theravia.For more information, call 1-844-884-5520.

This Medication Guide has been approved by the U.S. Food and Drug Administration.

Revised: 11/2023

INSTRUCTIONS FOR USE

SIKLOS (See – k – los)
(hydroxyurea)
tablets

Read this Instructions for Use before you start taking SIKLOS and each time you get a refill. There may be new information. This Instructions for Use does not take the place of talking to your healthcare provider about your medical condition or treatment. You and your healthcare provider should talk about SIKLOS when you start taking it and at regular checkups.

Important Information:

- Wash your hands with soap and water before and after handling SIKLOS tablets or bottles containing SIKLOS.
- Wear disposable gloves when handling SIKLOS tablets or bottles containing SIKLOS.
- Take SIKLOS 1 time a day at the same time each day.
- Powder spilled from a broken tablet should be wiped up right away with a damp disposable paper towel and thrown away in a closed container, such as a plastic bag to avoid harm to other people. The spill area should then be cleaned using a detergent solution followed by clean water.
- When the tablet is broken, avoid touching the broken surfaces.
- If contact with crushed tablets happens on the skin, wash the skin area right away and thoroughly with soap and water.
- If contact with crushed tablets happens in the eyes, flush the eyes thoroughly with water or isotonic eyewash used for that purpose for at least 15 minutes.

SIKLOS is supplied in 2 different strengths:

SIKLOS 100 mg tablethas one separation line (score line) and can be broken at this score line to provide smaller doses. Each 100 mg tablet can be divided into 2 equal parts (each part is 50 mg).

SIKLOS 1,000 mg tablethas three separation lines (score lines) and can be broken at these score lines to provide smaller doses. Each 1,000 mg tablet can be divided into 4 equal parts (each part is 250 mg).

SIKLOS tablet breaking instructions

You will need the following supplies to break a SIKLOS tablet:

- SIKLOS tablets
- A damp disposable paper towel
- A tablet cutter
- Disposable gloves

Step 1:Place a damp disposable paper towel on a flat surface where the tablets will be broken.

Step 2:Wash and dry your hands before handling SIKLOS tablets or bottles containing the tablets.

Step 3:Check your prescribed dose. You may need more than 1 tablet to get your prescribed dose.

Step 4:Put on disposable gloves.

Step 5:Remove the SIKLOS tablet out of the bottle needed to get your dose.

Step 6:Use your index fingers and thumbs to hold each end of the SIKLOS tablet.

SIKLOS 100 mg

side view

side view between fingers and thumbs

SIKLOS 1,000 mg

side view

side view between fingers and thumbs

Step 7:While holding the ends of the SIKLOS tablet, push down on the tablet to break the tablet on the score line to get your prescribed dose.
SIKLOS 100 mg tablets can be broken as:

Whole tablet

top view

side view

- 1/2 of a tablet for a dose of 50 mg of SIKLOS:

- a whole tablet for a dose of 100 mg of SIKLOS (no breaking needed):

SIKLOS 1,000 mg tablets can be broken as:

Whole tablet

Top view

side view

- 1/4 of a tablet for a dose of 250 mg of SIKLOS:

- 1/2 of a tablet for a dose of 500 mg of SIKLOS:

- 3/4 of a tablet for a dose of 750 mg of SIKLOS:

- a whole tablet for a dose of 1,000 mg of SIKLOS (no breaking needed):

Note: You may need to use a tablet cutter.

Step 8:Take your prescribed dose by swallowing it with a glass of water.
Important:If you have difficulty swallowing SIKLOS tablets, please stop here and follow the instructions below, "For people who cannot swallow SIKLOS tablets".

Step 9:Throw away the damp disposable paper towel in the trash. Pull off disposable gloves and throw away in the trash.

Wash and dry your hands.

Step 10:Store any unused broken tablets in the bottle and put the bottle back in the box. Broken tablets must be used within three months.

For people who cannot swallow SIKLOS tablets

You will need the following supplies to prepare and take your dose by dissolving the tablet:

- Your bottle of SIKLOS tablets
  - Note:If you need to break your tablets, use the SIKLOS Tablet Breaking Instructions aboveto get your prescribed dose beforeyou begin the steps below.
- A teaspoon
- Water to dissolve tablets

Step 1:Get your prescribed dose of SIKLOS tablets. Put your prescribed dose of SIKLOS tablets onto the teaspoon.

SIKLOS 100 mg tablet

SIKLOS 1,000 mg tablet (broken)

Step 2:Add a small amount of water to the teaspoon. The tablet dissolves within about 1 minute.

SIKLOS 100 mg tablet

SIKLOS 1,000 mg tablet (broken)

Step 3:Swallow the mixture right away.

Step 4:After you take your prescribed dose of SIKLOS tablets, drink a glass of water. When you are finished drinking a glass of water, continue to Step 9 and Step 10 above.

Storing your SIKLOS tablets:

- Store SIKLOS at room temperature between 68°F to 77°F (20°C to 25°C).
- Keep the SIKLOS bottle tightly closed.

Keep SIKLOS and all medicines out of the reach of children.

This Instructions for Use has been approved by the U.S. Food and Drug Administration.
Revised 11/2023

PRINCIPAL DISPLAY PANEL - 1000 mg Tablet Bottle Label

NDC 71770-120-30

Siklos®1,000 mg
(hydroxyurea) tablets

1,000 mg per tablet

ATTENTION PHARMACIST:
Each patient is required
to receive the enclosed
Medication Guide

30 tablets

RX Only.

Store at 20°C to 25°C (68°F to 77°F); excursions
permitted between 15°C and 30°C (59°F and 86°F)

WARNING: MYELOSUPPRESSION AND
MALIGNANCIES

Handle tablets with care.
Do not use or dispense before reading directions
and warnings in accompanying product
information.

Wear disposable gloves when handling Siklos®or
bottles containing Siklos®

Dosage and Use:See prescribing information.

Distributed by Medunik USA
Princeton, NJ, USA 08540

theravia

PRINCIPAL DISPLAY PANEL - 1,000 mg Tablet Bottle Carton

NDC 71770-120-30

Siklos®1,000 mg
(hydroxyurea)
tablets

1,000 mg per tablet

ATTENTION
PHARMACIST:
Each patient is
required to receive
the enclosed
Medication Guide

30 tablets

theravia

PRINCIPAL DISPLAY PANEL - 100 mg Tablet Bottle Label

Siklos®
100 mg
(hydroxyurea)
100 mg per tablet
60 tablets

NDC 71770-105-60
Store at 20°C to 25°C (68°F to 77°F)
Wear disposable gloves when handling Siklos®or bottles containing Siklos®
ATTENTION PHARMACIST:
Each patient is required to
receive the enclosed
Medication Guide

RX Only.
theravia

PRINCIPAL DISPLAY PANEL - 100 mg Tablet Bottle Carton

NDC 71770-105-60
Siklos®100 mg
(hydroxyurea)
tablets
100 mg per tablet

ATTENTION
PHARMACIST:
Each patient is
required to receive
the enclosed
Medication Guide

60 tablets

theravia